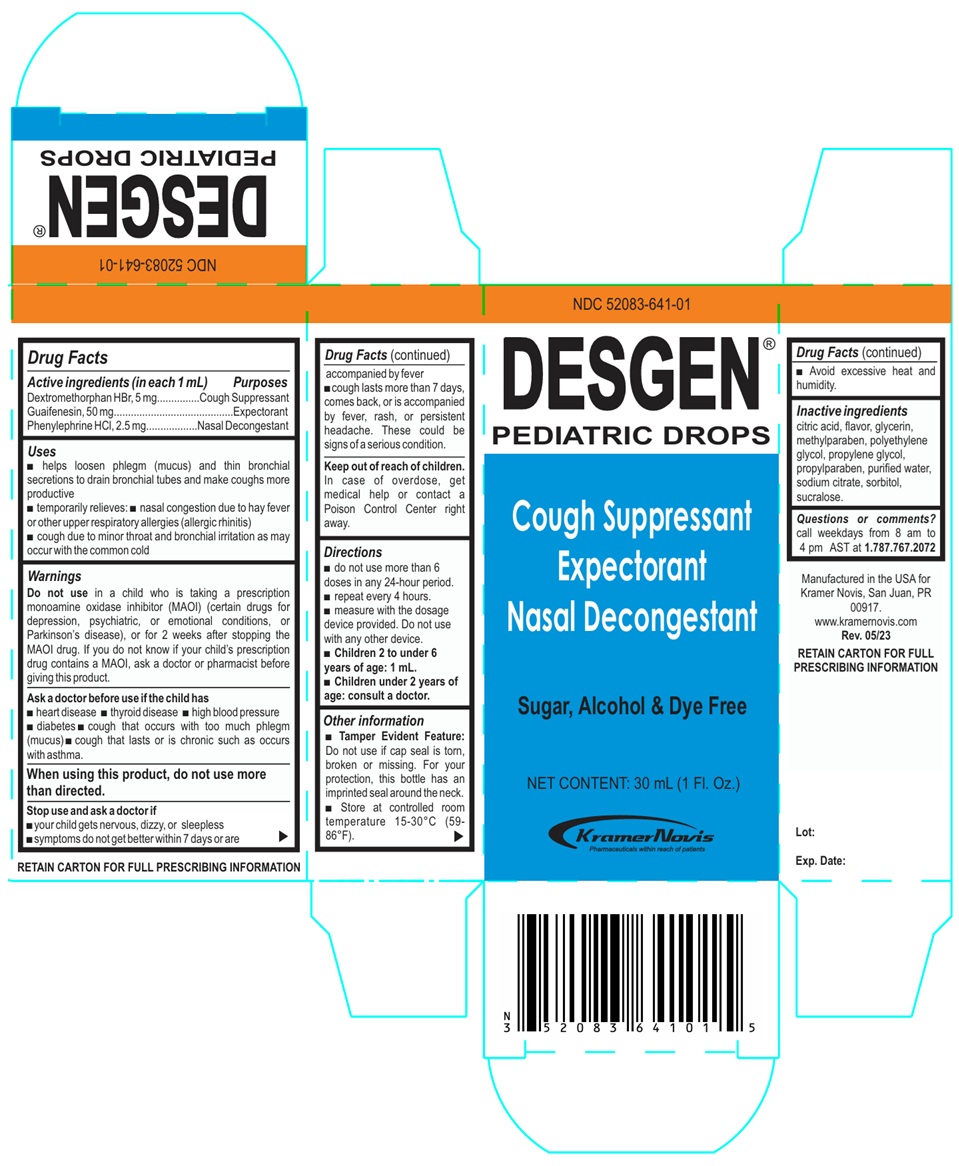 DRUG LABEL: Desgen
NDC: 52083-641 | Form: SOLUTION/ DROPS
Manufacturer: Kramer Novis
Category: otc | Type: HUMAN OTC DRUG LABEL
Date: 20251204

ACTIVE INGREDIENTS: DEXTROMETHORPHAN HYDROBROMIDE 5 mg/1 mL; GUAIFENESIN 50 mg/1 mL; PHENYLEPHRINE HYDROCHLORIDE 2.5 mg/1 mL
INACTIVE INGREDIENTS: CITRIC ACID MONOHYDRATE; GLYCERIN; METHYLPARABEN; POLYETHYLENE GLYCOL, UNSPECIFIED; PROPYLENE GLYCOL; PROPYLPARABEN; WATER; SODIUM CITRATE, UNSPECIFIED FORM; SORBITOL; SUCRALOSE

DESGEN® PEDIATRIC DROPS

Active ingredients (in each 1 mL)

Dextromethorphan HBr, 5 mg
Guaifenesin, 50 mg
Phenylephrine HCl, 2.5 mg

Purposes

Cough Suppressant
Expectorant
Nasal Decongestant

Uses

• helps loosen phlegm (mucus) and thin bronchial secretions to drain bronchial tubes and make coughs more productive
• temporarily relieves: • nasal congestion due to hay fever or other upper respiratory allergies (allergic rhinitis)
• cough due to minor throat and bronchial irritation as may occur with the common cold

Warnings

Do not use in a child who is taking a prescription monoamine oxidase inhibitor (MAOI) (certain drugs for depression, psychiatric, or emotional conditions, or Parkinson's disease), or for 2 weeks after stopping the MAOI drug. If you do not know if your child's prescription drug contains a MAOI, ask a doctor or pharmacist before giving this product.

Ask a doctor before use if the child has
• heart disease • thyroid disease • high blood pressure • diabetes • cough that occurs with too much phlegm (mucus) • cough that lasts or is chronic such as occurs with asthma.

When using this product, do not use more than directed.

Stop use and ask a doctor if
• your child gets nervous, dizzy, or sleepless
• symptoms do not get better within 7 days or are accompanied by fever
• cough lasts more than 7 days, comes back, or is accompanied by fever, rash, or persistent headache. These could be signs of a serious condition.

Keep out of reach of children. In case of overdose, get medical help or contact a Poison Control Center right away.

Directions

• do not use more than 6 doses in any 24-hour period.
• repeat every 4 hours.
• measure with the dosage device provided. Do not use with any other device.
• Children 2 to under 6 years of age: 1 mL.
• Children under 2 years of age: consult a doctor.

Other information

• Tamper Evident Feature: Do not use if cap seal is torn, broken or missing. For your protection, this bottle has an imprinted seal around the neck.
• Store at controlled room temperature 15-30°C (59-86°F).
• Avoid excessive heat and humidity.

Inactive ingredients

citric acid, flavor, glycerin, methylparaben, polyethylene glycol, propylene glycol, propylparaben, purified water, sodium citrate, sorbitol, sucralose.

Questions or comments?

call weekdays from 8 am to 4 pm AST at 1.787.767.2072

Cough Suppressant

Expectorant

Nasal Decongestant

Sugar, Alcohol & Dye Free

Kramer Novis
Pharmaceuticals within reach of patients

Manufactured in the USA for
Kramer Novis, San Juan, PR 00917.

www.kramernovis.com